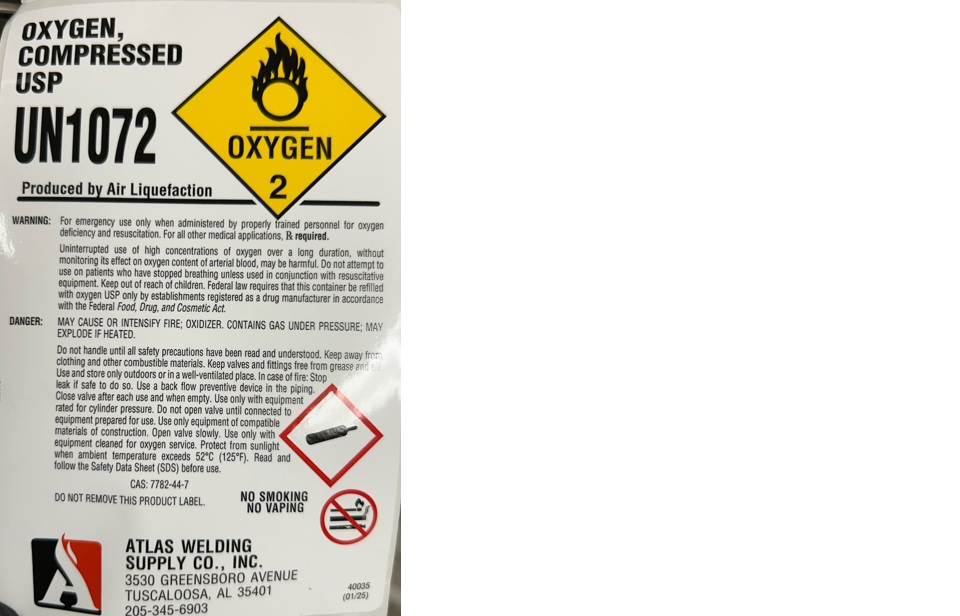 DRUG LABEL: Oxygen
NDC: 51051-011 | Form: GAS
Manufacturer: Atlas Welding Supply Company, Inc.
Category: animal | Type: PRESCRIPTION ANIMAL DRUG LABEL
Date: 20251223

ACTIVE INGREDIENTS: OXYGEN 990 mL/1 L

Oxygen

PACKAGE LABEL

OXYGEN, COMPRESSED USP
UN1072
Produced by Air Liquefaction
WARNING: For emergency use only when administered by properly trained personnel for oxygen deficiency and resuscitation. For all other medical applications, Rx required
Uninterrupted use of high concentrations of oxygen over a long duration, without monitoring its effect on oxygen content of arterial blood, may be harmful. Do not attempt to use on patients who have stopped breathing unless used in conjunction with resuscitative equipment. Keep out of reach of children. Federal law requires that this container be refilled with oxygen USP only by establishments registered as a drug manufacturer in accordance with the Federal Food, Drug, and Cosmetic Act.
DANGER: MAY CAUSE OR INTENSIFY FIRE; OXIDIZER. CONTAINS GAS UNDER PRESSURE; MAY EXPLODE IF HEATED.
Do not handle until all safety precautions have been read and understood. Keep away from clothing and other combustible materials. Keep valves and fittings free from grease and oil. Use and store only outdoors or in a well-ventilated place. In case of fire: Stop leak if safe to do so. Use a back flow preventive device in the piping. Close valve after each use and when empty. Use only with equipment rated for cylinder pressure. Do not open valve until connected to equipment prepared for use. Use only equipment of compatible materials of construction. Open valve slowly. Use only with equipment cleaned for oxygen service. Protect from sunlight when ambient temperature exceeds 52 C (125 F). Read and follow the Safety Data Sheet (SDS) before use.
CAS: 7782-44-7
DO NOT REMOVE THIS PRODUCT LABEL.
NO SMOKING
NO VAPING
ATLAS WELDING SUPPLY CO., INC.
3530 GREENSBORO AVENUE
TUSCALOOSA, AL 35401
205-345-6903